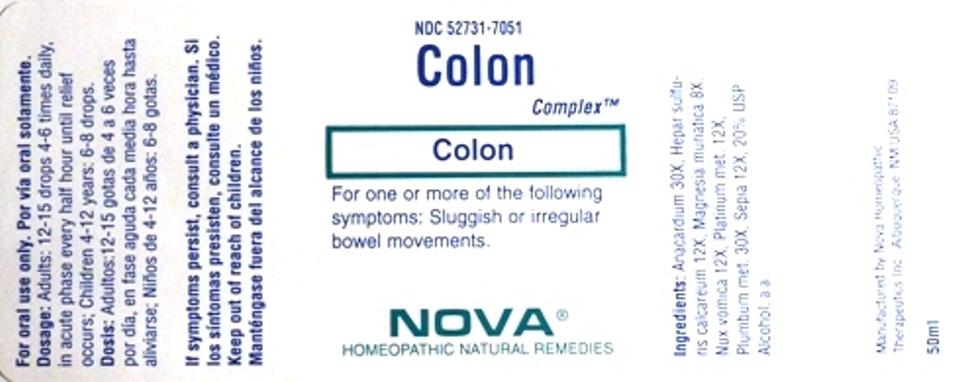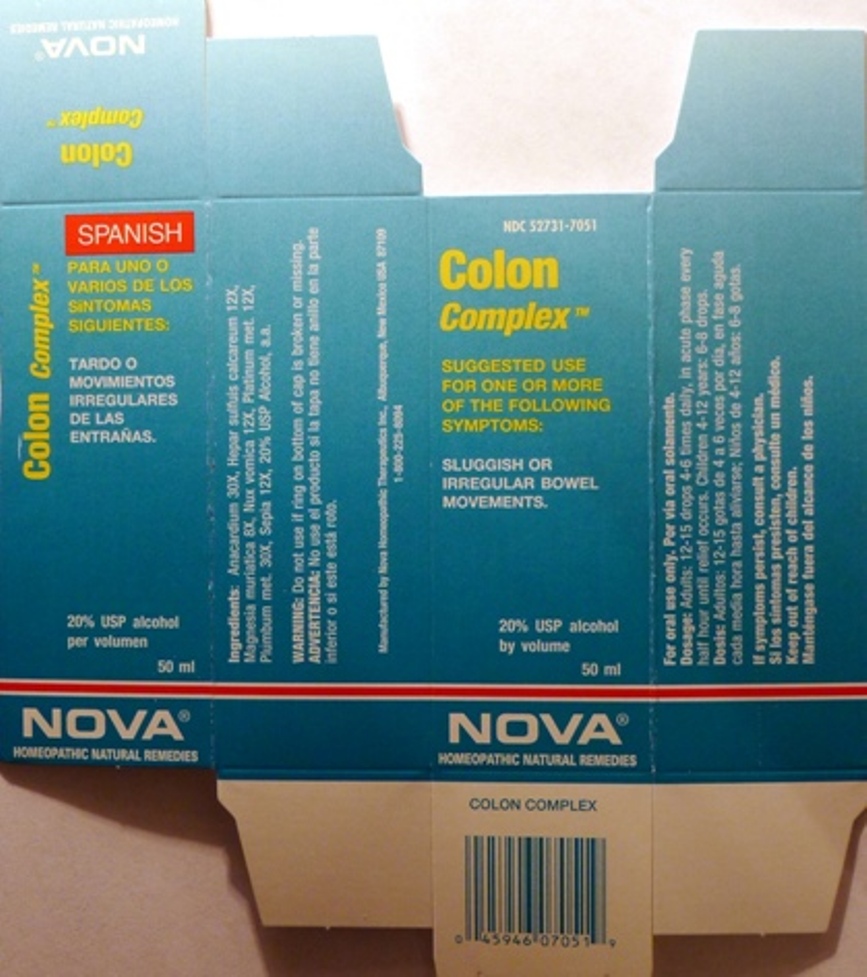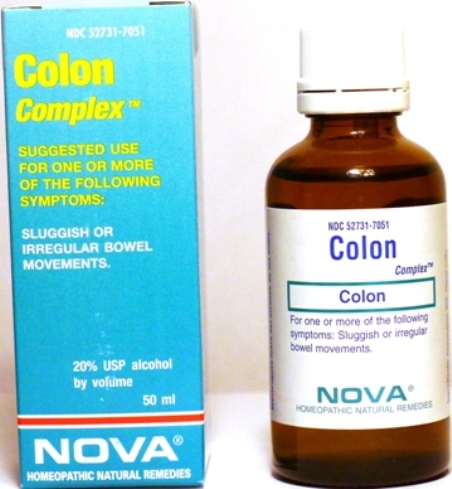 DRUG LABEL: Colon Complex
NDC: 52731-7051 | Form: LIQUID
Manufacturer: Nova Homeopathic Therapeutics, Inc.
Category: homeopathic | Type: HUMAN OTC DRUG LABEL
Date: 20110601

ACTIVE INGREDIENTS: SEMECARPUS ANACARDIUM JUICE 30 [hp_X]/1 mL; CALCIUM SULFIDE 12 [hp_X]/1 mL; MAGNESIUM CHLORIDE 8 [hp_X]/1 mL; STRYCHNOS NUX-VOMICA SEED 12 [hp_X]/1 mL; PLATINUM 12 [hp_X]/1 mL; LEAD 30 [hp_X]/1 mL; SEPIA OFFICINALIS JUICE 12 [hp_X]/1 mL
INACTIVE INGREDIENTS: ALCOHOL

Colon Complex

Purpose:

Suggested use for one or more of the following symptoms:

Sluggish or irregular bowel movements.

Usage and Dosage:

For oral use only.

DOSAGE AND ADMINISTRATION

Adults:
In Acute Phase:
12-15 drops, every half hour until relief occurs
When Relief Occurs:
12-15 drops, 4-6 times per day
Children 4-12 years:
6-8 drops, 4-6 times per day

Warnings:

Keep out of reach of children.

WARNINGS

If symptoms persist, consult a physician.
Do not use if ring on bottom of cap is broken or missing.

Active Ingredients:

Anacardium 30X, Hepar sulfuis calcareum 12X, Magnesia muriatica 8X, Nux vomica 12X, Platinum met. 12X, Plumbum met. 30X, Sepia 12X

Inactive Ingredients:

Alcohol, 20% USP

QUESTIONS

Manufactured by Nova Homeopathic Therapeutics Inc., Albuquerque, New Mexico USA 87109
1-800-225-8094

PACKAGE LABEL

Colon Complex Product

Colon Complex Bottle Label

Colon Complex Box